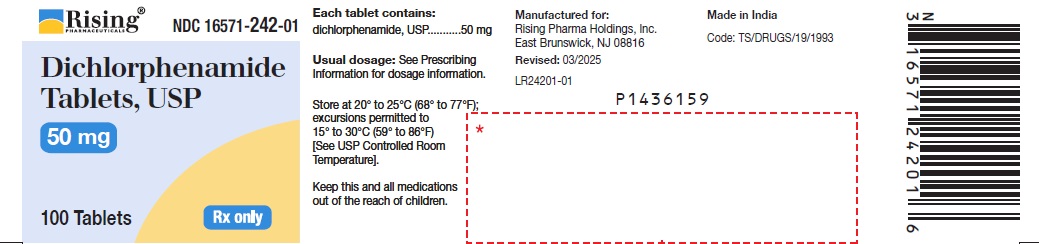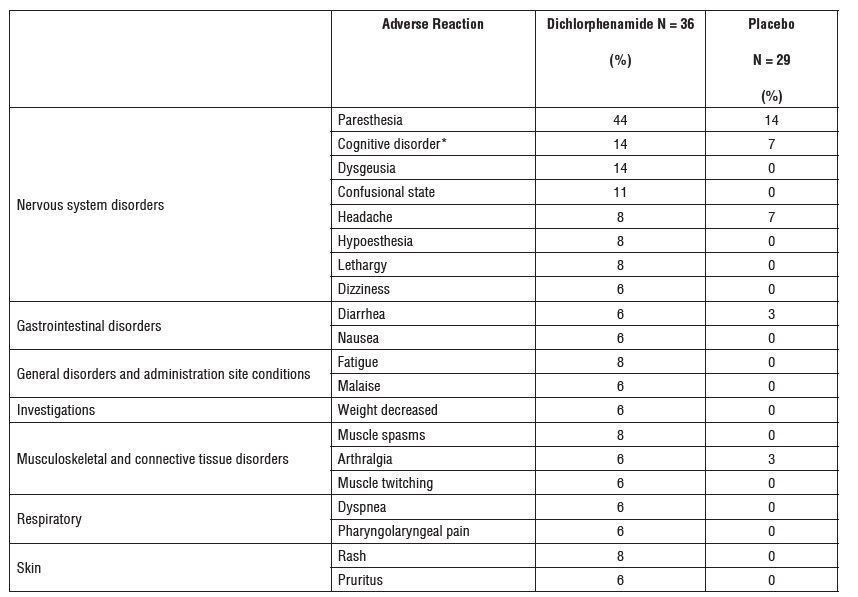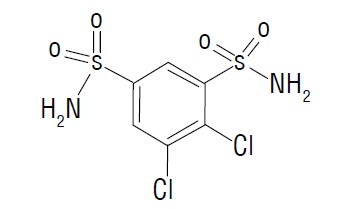 DRUG LABEL: Dichlorphenamide
NDC: 16571-242 | Form: TABLET
Manufacturer: Rising Pharma Holdings, Inc.
Category: prescription | Type: HUMAN PRESCRIPTION DRUG LABEL
Date: 20251125

ACTIVE INGREDIENTS: DICHLORPHENAMIDE 50 mg/1 1
INACTIVE INGREDIENTS: LACTOSE MONOHYDRATE; STARCH, CORN; SILICON DIOXIDE; MAGNESIUM STEARATE

HIGHLIGHTS OF PRESCRIBING INFORMATION

These highlights do not include all the information needed to use DICHLORPHENAMIDE TABLETS safely and effectively. See full prescribing information for DICHLORPHENAMIDE TABLETS.
DICHLORPHENAMIDE tablets, for oral use
Initial U.S. Approval: 1958

1 INDICATIONS AND USAGE

Dichlorphenamide tablets are an oral carbonic anhydrase inhibitor indicated for the treatment of primary hyperkalemic periodic paralysis, primary hypokalemic periodic paralysis, and related variants (1)

2 DOSAGE AND ADMINISTRATION

• Initiate dosing at 50 mg by mouth once or twice daily (2.1)
• Titrate up or down dose based on individual response (2.1)
• The minimum recommended dosage is 50 mg daily, and the maximum recommended dosage is 200 mg daily (2.1)
• Evaluate response to dichlorphenamide tablets after 2 months of treatment (2.2)

3 DOSAGE FORMS AND STRENGTHS

Tablets: 50 mg (3)

4 CONTRAINDICATIONS

- Hepatic insufficiency (4)
- Severe pulmonary obstruction (4)
- Hypersensitivity to dichlorphenamide or other sulfonamides (4)
- Concomitant use with high dose aspirin (4)

5 WARNINGS AND PRECAUTIONS

- Hypersensitivity and Other Life-Threatening Reactions: discontinue dichlorphenamide at the first appearance of skin rash or any sign of immune-mediated or idiosyncratic adverse reaction (5.1)
- Hypokalemia: baseline and periodic measurements of serum potassium are recommended; if hypokalemia develops or persists, consider reducing the dose or discontinuing dichlorphenamide and correcting potassium levels (5.3)
- Metabolic acidosis: baseline and periodic measurements of serum bicarbonate are recommended; if metabolic acidosis develops or persists, consider reducing the dose or discontinuing dichlorphenamide (5.4)
- Falls: consider reducing the dose or discontinuing dichlorphenamide in patients who experience falls (5.5)

6 ADVERSE REACTIONS

Most common adverse reactions (incidence at least 10% and greater than placebo) include paresthesias, cognitive disorder, dysgeusia, and confusional state (6.1)

To report SUSPECTED ADVERSE REACTIONS, contact Rising Pharma Holdings, Inc. at 1-844-874-7464, or FDA at 1-800-FDA-1088 or www.fda.gov/medwatch.

7 DRUG INTERACTIONS

Aspirin: anorexia, tachypnea, lethargy, and coma have been reported with concomitant use of dichlorphenamide and high-dose aspirin. The concomitant use of dichlorphenamide tablets and high-dose aspirin is contraindicated. Dichlorphenamide tablets should be used with caution in patients receiving lower doses of aspirin (4, 5.2, 7.1)

8 USE IN SPECIFIC POPULATIONS

Pregnancy: Based on animal data, may cause fetal harm (8.1)

FULL PRESCRIBING INFORMATION

1 INDICATIONS AND USAGE

Dichlorphenamide tablets are indicated for the treatment of primary hyperkalemic periodic paralysis, primary hypokalemic periodic paralysis, and related variants.

2 DOSAGE AND ADMINISTRATION

2.1 Dosage Information

Initiate dosing at 50 mg by mouth once or twice daily. The dosage may be increased or decreased based on individual response, at weekly intervals (or sooner in case of adverse reaction). The minimum recommended total daily dosage is 50 mg, and the maximum recommended total daily dosage is 200 mg.

2.2 Monitoring to Assess Effectiveness

Primary hyperkalemic periodic paralysis, primary hypokalemic periodic paralysis, and related variants are a heterogeneous group of conditions, for which the response to dichlorphenamide may vary. Therefore, prescribers should evaluate the patient's response to dichlorphenamide after 2 months of treatment to decide whether dichlorphenamide tablets should be continued.

2.3 Monitoring to Assess Safety

Baseline and periodic measurements of serum potassium and sodium bicarbonate during dichlorphenamide treatment is recommended [see Warnings and Precautions (5.3, 5.4)].

3 DOSAGE FORMS AND STRENGTHS

Dichlorphenamide tablet USP, 50 mg is white colored flat round tablet with beveled edge, scored on one side and engraved with "C" above and "43" below on other side.

4 CONTRAINDICATIONS

Dichlorphenamide is contraindicated in the following circumstances:

- Hypersensitivity to dichlorphenamide or other sulfonamides [see Warnings and Precautions (5.1)]
- Concomitant use of dichlorphenamide and high dose aspirin [see Warnings and Precautions (5.2) and Drug Interactions (7.1)]
- Severe pulmonary disease, limiting compensation to metabolic acidosis caused by dichlorphenamide [see Warnings and Precautions (5.4)]
- Hepatic insufficiency: dichlorphenamide may aggravate hepatic encephalopathy.

5 WARNINGS AND PRECAUTIONS

5.1 Hypersensitivity and Other Life-Threatening Reactions

Fatalities associated with the administration of sulfonamides have occurred because of adverse reactions including Stevens-Johnson syndrome, toxic epidermal necrolysis, fulminant hepatic necrosis, agranulocytosis, aplastic anemia and other blood dyscrasias. Pulmonary involvement can occur in isolation or as part of a systemic reaction.

Dichlorphenamide should be discontinued at the first appearance of skin rash or any sign of immune-mediated or other life-threatening adverse reaction.

5.2 Concomitant Use of Aspirin or Other Salicylates

Carbonic anhydrase inhibitors, including dichlorphenamide, can cause metabolic acidosis [see Warnings and Precautions (5.4)], which can increase the risk of salicylate toxicity. Anorexia, tachypnea, lethargy, and coma have been reported with concomitant use of dichlorphenamide and high-dose aspirin. Therefore, the concomitant use of dichlorphenamide and high-dose aspirin is contraindicated. Patients with concomitant use of dichlorphenamide and low-dose aspirin should be carefully monitored.

5.3 Hypokalemia

Dichlorphenamide increases potassium excretion and can cause hypokalemia. The risk of hypokalemia is greater when dichlorphenamide is used in patients with conditions associated with hypokalemia (e.g., adrenocortical excess, renal tubular acidosis type 1 and 2), and in patients receiving other drugs that may cause hypokalemia [see Drug Interactions (7.3)].

Baseline and periodic measurements of serum potassium during dichlorphenamide treatment is recommended.

If hypokalemia develops or persists, consideration should be given to reducing the dose or discontinuing dichlorphenamide and correction of potassium levels.

5.4 Metabolic Acidosis

Dichlorphenamide can cause hyperchloremic non-anion gap metabolic acidosis. Concomitant use of dichlorphenamide with other drugs that cause metabolic acidosis may increase the severity of acidosis. Concomitant use of dichlorphenamide in compensated patients with respiratory acidosis, such as in advanced lung diseases, may lead to respiratory decompensation.

Baseline and periodic measurements of serum bicarbonate during dichlorphenamide treatment are recommended.

If metabolic acidosis develops or persists, consideration should be given to reducing the dose or discontinuing dichlorphenamide [see Drug Interactions (7.4)].

5.5 Falls

Dichlorphenamide increases the risk of falls. The risk of falls is greater in the elderly and with higher doses of dichlorphenamide. Consider dose reduction or discontinuation of dichlorphenamide in patients who experience falls while treated with dichlorphenamide.

6 ADVERSE REACTIONS

The following serious adverse reactions are described elsewhere in labeling:

- Hypersensitivity and Other Life-Threatening Reactions [see Warnings and Precautions (5.1)]
- Hypokalemia [see Warnings and Precautions (5.3)]
- Metabolic Acidosis [see Warnings and Precautions (5.4)]
- Falls [see Warnings and Precautions (5.5)]

6.1 Clinical Trials Experience

Because clinical trials are conducted under widely varying conditions, adverse reaction rates observed in the clinical trials of a drug cannot be directly compared to rates in the clinical trials of another drug and may not reflect the rates observed in practice.

In a 9-week randomized controlled trial in adults with hyperkalemic or hypokalemic periodic paralysis (Study 1), the most common adverse reactions in patients treated with dichlorphenamide, with rates greater than placebo, were paresthesia, cognitive disorder, dysgeusia, and confusional state. The mean dose of dichlorphenamide was 94 mg/day in patients with hypokalemic periodic paralysis and 82 mg/day in patients with hyperkalemic periodic paralysis.

Table 1 lists the incidence of adverse reactions that occurred in ≥ 5% of patients treated with dichlorphenamide and more commonly than in patients treated with placebo in Study 1.

Table 1: Adverse Reactions in Patients Treated with dichlorphenamide with Incidence > 5% and more common than in Patients Treated with Placebo in Study 1

*Cognitive disorder combined cases with the preferred terms of cognitive disorder, disturbance in attention, and mental impairment.

6.2 Postmarketing Experience

Adverse reactions have been identified during postapproval use of dichlorphenamide. Because these reactions are reported voluntarily from a population of uncertain size, it is not always possible to reliably estimate their frequency or establish a causal relationship to drug exposure.

The following are adverse reactions which have been reported during postapproval use of dichlorphenamide and were serious or are not reported in the previous section of labeling [see Clinical Trials Experience (6.1)]: amnesia, cardiac failure, condition aggravated, convulsion, hallucination, nephrolithiasis, pancytopenia, psychotic disorder, renal tubular necrosis, stupor, syncope, tremor.

7 DRUG INTERACTIONS

7.1 Aspirin and Other Salicylates

Carbonic anhydrase inhibitors, including dichlorphenamide, can cause metabolic acidosis [see Warnings and Precautions (5.2, 5.4)], which can increase the risk of salicylate toxicity. Anorexia, tachypnea, lethargy, and coma have been reported with concomitant use of dichlorphenamide and high-dose aspirin. Therefore, concomitant use of dichlorphenamide and high-dose aspirin is contraindicated. Patients with concomitant use of dichlorphenamide and low-dose aspirin should be carefully monitored [see Contraindications (4) and Warnings and Precautions (5.2)].

7.2 Drugs that are Substrates of Organic Anion Transporter1 (OAT1)

In vitro, dichlorphenamide is an inhibitor of OAT1 transporters. The concomitant administration of dichlorphenamide may increase the plasma exposures of OAT1 substrates. Use of dichlorphenamide with drugs that are sensitive to OAT1 inhibition (e.g., methotrexate, famotidine, oseltamivir) is not recommended [see Clinical Pharmacology (12.3)].

7.3 Drugs that Cause Hypokalemia

The risk of hypokalemia is greater with coadministration of dichlorphenamide and other drugs that can cause hypokalemia (e.g., loop diuretics, thiazide diuretics, laxatives, antifungals, penicillins, and theophylline) [see Warnings and Precautions (5.3)].

7.4 Drugs that Cause Metabolic Acidosis

Coadministration of dichlorphenamide and other drugs that can cause metabolic acidosis may increase the severity of the acidosis [see Warnings and Precautions (5.4)].

7.5 Drugs that are Inhibitors of OAT1 or OAT3

An in vitro transporter study indicated that dichlorphenamide is a substrate of human transporters OAT1 and OAT3 [see Clinical Pharmacology (12.3)]. Therefore, signs of dichlorphenamide toxicity should be monitored when administered with OAT1 or OAT3 inhibitors.

8 USE IN SPECIFIC POPULATIONS

8.1 Pregnancy

Risk Summary

There are no adequate data on the developmental risk associated with the use of dichlorphenamide in pregnant women. A no-effect dose has not been established. Dichlorphenamide was teratogenic when administered orally to pregnant rats.

The background risk of major birth defects and miscarriage for the indicated population is unknown. In the U.S. general population, the estimated background risk of major birth defects and miscarriage in clinically recognized pregnancies is 2% to 4%, and 15% to 20%, respectively.

Clinical Considerations

Fetal/Neonatal adverse reactions
Dichlorphenamide treatment can cause metabolic acidosis [see Warnings and Precautions (5.4)]. The effect of dichlorphenamide-induced metabolic acidosis has not been studied in pregnancy; however, metabolic acidosis in pregnancy (due to other causes) can cause decreased fetal growth, decreased fetal oxygenation, and fetal death, and may affect the fetus’ ability to tolerate labor. Pregnant patients should be monitored for metabolic acidosis and treated as in the nonpregnant state. Newborns of mothers treated with dichlorphenamide should be monitored for metabolic acidosis because of possible occurrence of transient metabolic acidosis following birth.

Labor or Delivery
Although the effect of dichlorphenamide on labor and delivery in humans has not been established, the development of dichlorphenamide-induced metabolic acidosis in the mother and/or in the fetus might affect the fetus’ ability to tolerate labor.

Data

Animal Data
Teratogenic effects (fetal limb reduction defects) were reported following oral administration of dichlorphenamide to pregnant rats during organogenesis at 350 mg/kg, or 17 times the maximum recommended human dose (200 mg/day) on a body surface area (mg/m^2) basis. A no-effect dose for adverse effects on embryofetal development has not been established.

8.2 Lactation

Risk Summary

There are no data on the presence of dichlorphenamide in human milk, the effects on the breastfed infant, or the effects on milk production.

The developmental and health benefits of breastfeeding should be considered along with the mother’s clinical need for dichlorphenamide and any potential adverse effects on the breastfed infant from dichlorphenamide or from the underlying maternal condition.

8.4 Pediatric Use

Safety and effectiveness of dichlorphenamide in pediatric patients have not been established.

8.5 Geriatric Use

The risk of falls and of metabolic acidosis are greater in elderly patients [see Warnings and Precautions (5.4, 5.5)].

10 OVERDOSAGE

Symptoms of overdosage or toxicity may include drowsiness, anorexia, nausea, vomiting, dizziness, ataxia, tremor, and tinnitus.

In the event of overdosage, induce emesis or perform gastric lavage. The electrolyte disturbances most likely to be encountered from overdosage are hypokalemia and hyperchloremic metabolic acidosis.

11 DESCRIPTION

Dichlorphenamide tablets USP contain dichlorphenamide, an oral carbonic anhydrase inhibitor. Dichlorphenamide USP, a dichlorinated benzenedisulfonamide, is known chemically as 4, 5– dichloro- 1,3-benzenedisulfonamide.

Its empirical formula is C6H6Cl2N2O4S2 and its structural formula is:

Dichlorphenamide USP is a white or practically white crystalline powder with a molecular weight of 305.16. It is soluble in 10% w/v sodium hydroxide solution, sparingly soluble in 10% w/v sodium carbonate solution and very slightly to practically insoluble in water.

Dichlorphenamide tablets USP are supplied as tablets, for oral administration, each containing 50 mg dichlorphenamide USP. Inactive ingredients are colloidal silicon dioxide, lactose monohydrate, magnesium stearate and pregelatinized starch.

12 CLINICAL PHARMACOLOGY

12.1 Mechanism of Action

Dichlorphenamide is a carbonic anhydrase inhibitor. However, the precise mechanism by which dichlorphenamide exerts its therapeutic effects in patients with primary periodic paralysis is unknown.

12.2 Pharmacodynamics

Dichlorphenamide can cause metabolic acidosis, which can increase the risk of salicylate toxicity with coadministration [see Warnings and Precautions (5.2)]. Dichlorphenamide-induced metabolic acidosis can also increase in severity with coadministration of other drugs that cause metabolic acidosis [see Warnings and Precautions (5.4)].

12.3 Pharmacokinetics

After single-dose administration in healthy subjects in fasted state, dichlorphenamide C max and AUC increased in a dose-proportional manner within the range of 25 mg to 400 mg (2 times the maximum recommended dose). The steady-state is expected to be achieved within 10 days of twice-daily dosing.

Absorption

The median time to reach maximum concentration (T max) of dichlorphenamide was about 1.5 to 3 hours postdose after both single and multiple dose administrations.

Distribution

The plasma protein binding of dichlorphenamide is approximately 88%.

Elimination

Following a single-dose administration, mean terminal half-life was in the range of 32 to 66 hours.

Metabolism

Dichlorphenamide is not a substrate for CYP1A2, CYP2B6, CYP2C8, CYP2C9, CYP2C19, CYP2D6 and CYP3A4 isoforms when tested in vitro.

Drug Interaction Studies

In vitro Assessment of Drug Interactions

Drug-Metabolizing Enzyme Inhibition

Dichlorphenamide is not an inhibitor for CYP1A2, 2B6, 2C8, 2C9, 2C19, 2D6, or 3A4 enzymes when tested in vitro.

Drug-Metabolizing Enzyme Induction

Dichlorphenamide is not an inducer for CYP1A2, 2B6, or 3A4 enzymes when tested in vitro.

In vitro Assessment of Transporter-Drug Interactions

Dichlorphenamide is neither a substrate nor inhibitor for p-gp, BCRP, OATP1B1, OATP1B3, OAT2, OAT4, OCT1, OCT2, MATE1, or MATE2-K when tested in vitro.

Dichlorphenamide is not an inhibitor of OAT3, but is an inhibitor of OAT1 based on in vitro studies [see Drug Interactions (7.4)].

Dichlorphenamide is a substrate for transporters OAT1 and OAT3 based on in vitro studies [see Drug Interactions (7.2)].

In Vivo Drug Interactions
The use of dichlorphenamide in combination with high-dose aspirin is contraindicated as it may lead to salicylate toxicity. The mechanism(s) of this interaction is not known.

Specific Populations

Geriatrics
The pharmacokinetics of dichlorphenamide in the elderly has not been determined.

13 NONCLINICAL TOXICOLOGY

13.1 Carcinogenesis, Mutagenesis, Impairment of Fertility

Carcinogenesis

Studies to assess the carcinogenic potential of dichlorphenamide have not been conducted.

Mutagenesis

Studies to assess the genotoxicity of dichlorphenamide have not been conducted.

Impairment of Fertility

Studies to assess the effects of dichlorphenamide on fertility have not been conducted.

14 CLINICAL STUDIES

The efficacy of dichlorphenamide tablets was evaluated in two clinical studies, Study 1 and Study 2.

Study 1

Study 1 was a 9-week, double-blind, placebo-controlled multi-center study. Study 1 consisted of two substudies: a substudy in patients with hypokalemic periodic paralysis (n=44), and a substudy in patients with hyperkalemic periodic paralysis (n=21). The primary efficacy endpoint in both substudies was the average number of self-reported attacks of muscle weakness per week over the final 8 weeks of the trial. Withdrawal from the study for acute severe worsening (increase in attack frequency or severity) was also assessed as an endpoint.

In Study 1, the dose of dichlorphenamide tablets was 50 mg b.i.d. for treatment-naïve patients. Patients already on dichlorphenamide prior to the study continued on the same dose while on dichlorphenamide during the study. In patients taking acetazolamide prior to the study, the dose of dichlorphenamide was set at 20% of the acetazolamide dose. Dose reduction for tolerability was permitted.

Hypokalemic Periodic Paralysis Substudy of Study 1

In the hypokalemic periodic paralysis substudy, median age of patients was 45 years and 73% of patients were male. Patients treated with dichlorphenamide (n=24) had 2.2 fewer attacks per week than patients (n=20) treated with placebo (p=0.02). None of the patients randomized to dichlorphenamide reached the endpoint of withdrawal from the study for acute worsening, vs. five patients randomized to placebo. The mean dose of dichlorphenamide at Week 9 was 94 mg/day.

Hyperkalemic Periodic Paralysis Substudy of Study 1

In the Hyperkalemic Periodic Paralysis substudy, median age of patients was 43 years and 43% of patients were male. During the double-blind treatment period, patients treated with dichlorphenamide (n=12) had 3.9 fewer attacks per week than patients (n=9) treated with placebo (p=0.08). None of the patients randomized to dichlorphenamide reached the endpoint of withdrawal from the study for acute worsening, vs. two patients randomized to placebo. The mean dose of dichlorphenamide at Week 9 was 82 mg/day.

Study 2

Study 2 was a 35-week, double-blind, placebo-controlled, multi-center, two-period crossover study. Study 2 also consisted of two substudies: a substudy in patients with hypokalemic periodic paralysis (n=42), and a substudy in patients with hyperkalemic periodic paralysis (n=31), including patients with Paramyotonia Congenita. The primary endpoint in the hypokalemic periodic paralysis substudy was the incidence of acute intolerable worsening (based on attack frequency or severity) necessitating withdrawal. The primary endpoint in the hyperkalemic periodic paralysis substudy was the average number of self-reported attacks of muscle weakness per week. Dosing was determined similarly to Study 1.

Hypokalemic Periodic Paralysis Substudy of Study 2

The hypokalemic periodic paralysis substudy included patients with a mean age of 38 years; 79% of patients were male. Acute intolerable worsening was observed in 2 patients on dichlorphenamide vs. 11 patients on placebo (p=0.02). The mean dose of dichlorphenamide at the end of the study was 96 mg/day.

Hyperkalemic Periodic Paralysis Substudy of Study 2

The hyperkalemic periodic paralysis substudy included patients with a mean age of 37 years; and 79% of patients were male. Patients treated had 2.3 fewer attacks per week on dichlorphenamide than on placebo (p=0.006). The mean dose of dichlorphenamide at the end of the study was 73 mg/day.

16 HOW SUPPLIED/STORAGE AND HANDLING

Each dichlorphenamide tablet USP, 50 mg is white colored flat round tablet with beveled edge, scored on one side and engraved with "C" above and "43" below on other side. They are supplied as follows:

Bottles of 100.............................................NDC 16571-242-01

Store at 20° to 25°C (68° to 77°F); excursions permitted to 15° to 30°C (59° to 86°F) [See USP Controlled Room Temperature].

17 PATIENT COUNSELING INFORMATION

Worsening of Symptoms
Advise patients to notify their physician if they experience acute worsening of symptoms of periodic paralysis.

Hypersensitivity and Other Life-Threatening Reactions
Inform patients that hypersensitivity and immune mediated reactions can occur with dichlorphenamide, and could be fatal. Advise patients to discontinue dichlorphenamide and notify their healthcare provider immediately if they develop a rash or signs and symptoms of anaphylaxis or other life-threatening reactions [see Warnings and Precautions (5.1)].

Drug Interactions
Instruct patients to notify their healthcare provider of all of the drugs and over-the-counter medications that they take and to not take aspirin or other salicylates without first discussing with their healthcare provider [see Drug Interactions (7.1, 7.2, 7.3, 7.4)].

Metabolic Acidosis
Instruct patients to contact their healthcare provider immediately if they develop possible manifestations of metabolic acidosis (e.g., fast breathing, fatigue/tiredness, loss of appetite, or irregular heart beat or palpitations) [see Warnings and Precautions (5.4)].

Falls
Inform patients that dichlorphenamide can increase their risk of falls [see Warnings and Precautions (5.5)].

Cognitive Impairment
Advise patients to notify their healthcare provider if they experience symptoms of cognitive impairment including confusion and memory lapse [see Adverse Reactions (6.1)].

Driving and Operating Machinery
Dichlorphenamide may cause drowsiness/fatigue in some patients [see Adverse Reactions (6.1)]. Caution patients on the potential for impaired ability to drive and operate machinery.

Manufactured for:

Rising Pharma Holdings, Inc.

East Brunswick, NJ 08816

Made in India

Code: TS/DRUGS/19/1993

Revised: 03/2025

PIR24201-01

PRINCIPAL DISPLAY PANEL

Dichlorphenamide tablet USP 50mg
NDC 16571-242-01